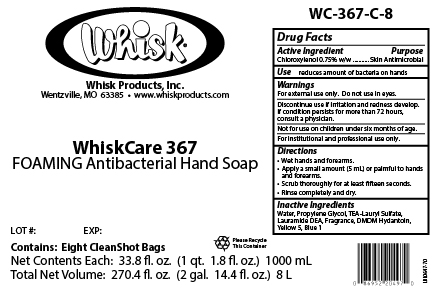 DRUG LABEL: WhiskCare 367
NDC: 65585-568 | Form: SOAP
Manufacturer: Whisk Products, Inc.
Category: otc | Type: HUMAN OTC DRUG LABEL
Date: 20240222

ACTIVE INGREDIENTS: CHLOROXYLENOL 7.5 mg/1 mL
INACTIVE INGREDIENTS: FD&C BLUE NO. 1; PROPYLENE GLYCOL; DMDM HYDANTOIN; LAURIC DIETHANOLAMIDE; WATER; TRIETHANOLAMINE LAURYL SULFATE; FD&C YELLOW NO. 5

WhiskCare 367

Active Ingredient

Chloroxylenol 0.75% w/w

Purpose

Skin Antimicrobial

Use

reduces amount of bacteria on hands

Warnings

For external use only. Do not use in eyes.

Discontinue use if irritation and redness develop. If condition persists for more than 72 hours, consult a physician.

KEEP OUT OF REACH OF CHILDREN

Not for use on children under six months of age.

For institutional and professional use only.

Directions

- Wet hands and forearms.
- Apply a small amount (5 mL) or palmful to hands and forearms.
- Scrub thoroughly for at least fifteen seconds.
- Rinse completely and dry.

Inactive Ingredients

Water, Propylene Glycol, TEA-Lauryl Sulfate, Lauramide DEA, Fragrance, DMDM Hydantoin, Yellow 5, Blue 1